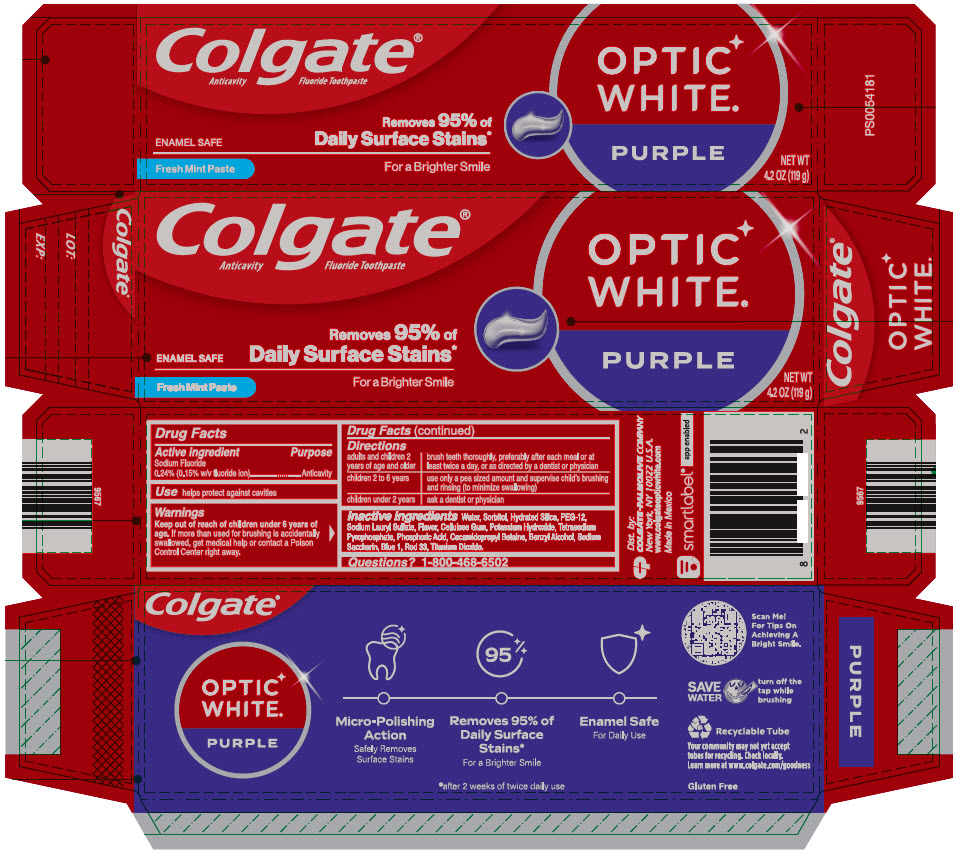 DRUG LABEL: TP COL OW Purple
NDC: 65954-825 | Form: PASTE, DENTIFRICE
Manufacturer: Mission Hills, S.A. de C.V.
Category: otc | Type: HUMAN OTC DRUG LABEL
Date: 20240912

ACTIVE INGREDIENTS: SODIUM FLUORIDE 1.1 mg/1 g
INACTIVE INGREDIENTS: WATER; HYDRATED SILICA; SORBITOL; POTASSIUM HYDROXIDE; POLYETHYLENE GLYCOL 600; PHOSPHORIC ACID; SODIUM PYROPHOSPHATE; SODIUM LAURYL SULFATE; CARBOXYMETHYLCELLULOSE SODIUM, UNSPECIFIED; COCAMIDOPROPYL BETAINE; SACCHARIN SODIUM; XANTHAN GUM; BENZYL ALCOHOL; D&C RED NO. 33; FD&C BLUE NO. 1; TITANIUM DIOXIDE

TP COL OW Purple

Drug Facts

Active ingredient

Sodium Fluoride 0.24% (0.15% w/v fluoride Ion)

Purpose

Anticavity

Use

helps protect against cavities

Warnings

Keep out of reach of children under 6 years of age. If more than used for brushing is accidentally swallowed, get medical help or contact a Poison Contol Center right away.

Directions

adults and children 2 years of age and older | brush teeth throughly, preferably after each meal or at least twice a day, or as directed by a dentist or physician
children 2 to 6 years | use only a pea sized amount and supervise child's brushing and rinsing (to minimize swallowing)
children under 2 years | ask a dentist or physician

Inactive Ingredients

Water, Sorbitol, Hydrated Silica, PEG-12, Sodium Lauryl Sulfate, Flavor, Cellulose Gum, Potassium Hydroxide, Tetrasodium Pyrophosphate, Phosphoric Acid, Cocamidopropyl Betaine, Benzyl Alcohol, Sodium Saccharin, Blue 1, Red 33, Titanium Dioxide.

Questions?

1-800-468-6502

Dist. by:
COLGATE-PALMOLIVE COMPANY
New York, NY 10022 U.S.A.

PRINCIPAL DISPLAY PANEL - 119 g Tube Carton

Colgate®
Anticavity Fluoride Toothpaste

ENAMEL SAFE

Removes 95% of
Daily Surface Stains*

Fresh Mint Paste

For a Brighter Smile

OPTIC
WHITE®

PURPLE

NET WT
4.2 OZ (119 g)